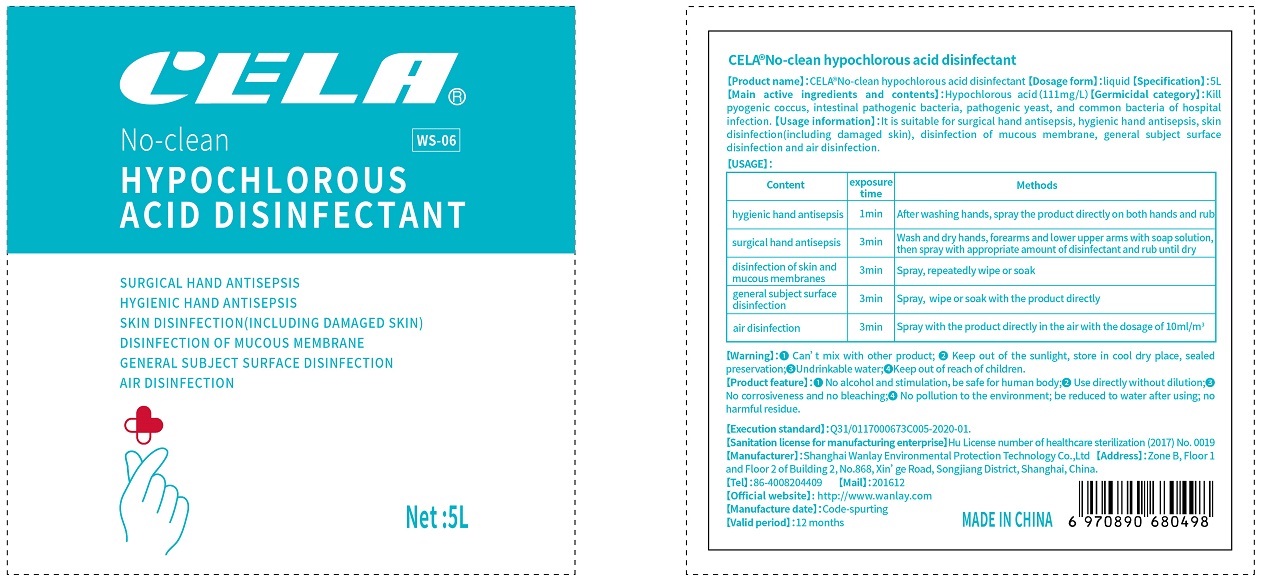 DRUG LABEL: CELA No-clean hypochlorous acid disinfectant
NDC: 75318-0106 | Form: LIQUID
Manufacturer: Shanghai Wanlay Environmental Protection Technology Co., Ltd.
Category: otc | Type: HUMAN OTC DRUG LABEL
Date: 20201223

ACTIVE INGREDIENTS: HYPOCHLOROUS ACID 555 mg/5 L
INACTIVE INGREDIENTS: WATER; SODIUM CHLORIDE

Wanlay, CELA disinfectant, Liquid, 5L-C

Active Ingredient(s)

Hypochlorous acid 111 mg/L. Purpose: Kill pyogenic coccus, intestinal pathogenic bacteria, pathogenic yeast, and common bacteria of hospital infection.

Purpose

It is suitable for surgical hand antisepsis, hygienic hand antisepsis, skin disinfection (including damaged skin), disinfection of mucous membrane, general subject surface disinfection and air disinfection.

Use

It is suitable for surgical hand antisepsis, hygienic hand antisepsis, skin disinfection (including damaged skin), disinfection of mucous membrane, general subject surface disinfection and air disinfection.

Warnings

External Use Only.

Keep out of reach children.

❶ Can’t mix with other product;

❷ Keep out of the sunlight, store in cool dry place, sealed preservation;

❸ Undrinkable water.

Do not use

- on children less than 2 months of age
- on open skin wounds
- mixing this product with other disinfectants

When using this product keep out of eyes, ears, and mouth.

In case of contact with eyes, rinse eyes thoroughly with water.

This product is for external use. It should not be taken orally.

This product has a certain corrosive effect on metal objects other than stainless steel, and should be used with caution.

When sterilizing articles containing more organic objects, they should be completely removed and then disinfected.

Use with caution for those with sensitive skin.

Do not mix this product with other disinfectants.

Stop use and ask a doctor if irritation or rash occurs. These may be signs of a serious condition.

Other information

Storage: place it in a normal temperature and light-shielded environment.

Directions

Content | exposure time | Methods
hygienic hand antisepsis | 1min | After washing hands, spray the product directly on both hands and rub
surgical hand antisepsis | 3min | Wash and dry hands, forearms and lower upper arms with soap solution, then spray with appropriate amount of disinfectant and rub until dry
disinfection of skin and mucous membranes | 3min | Spray, repeatedly wipe or soak
general subject surface disinfection | 3min | spray, wipe or soak with the product directly
air disinfection | 30min | spray with the product directly in the air with the dosage of 10ml/m3

Inactive ingredients

Sodium chloride, Water